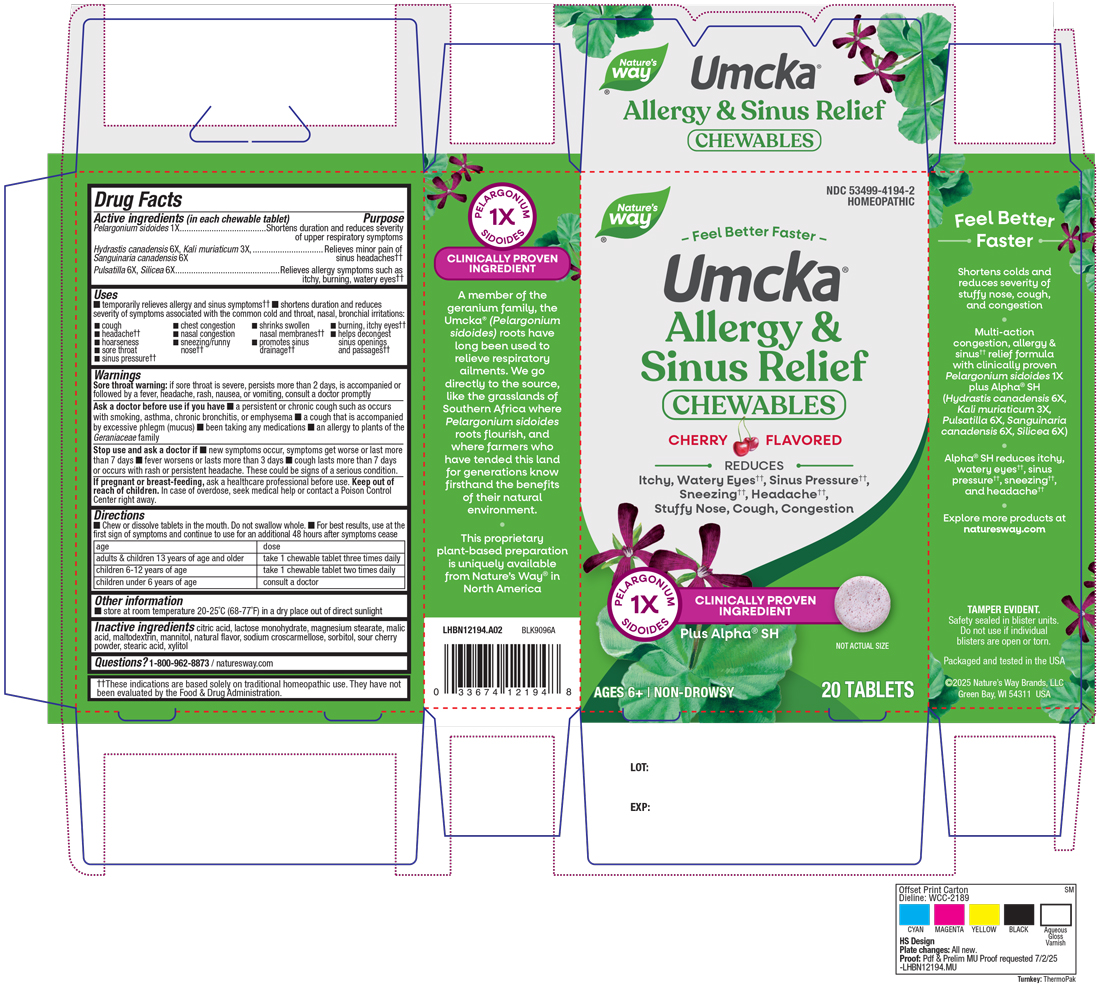 DRUG LABEL: Allergy and Sinus Relief
NDC: 53499-4194 | Form: TABLET, CHEWABLE
Manufacturer: Schwabe North American, Inc.
Category: homeopathic | Type: HUMAN OTC DRUG LABEL
Date: 20250825

ACTIVE INGREDIENTS: PELARGONIUM SIDOIDES ROOT 1 [hp_X]/1 1; HYDRASTIS CANADENSIS WHOLE 6 [hp_X]/1 1; POTASSIUM CHLORIDE 3 [hp_X]/1 1; SANGUINARIA CANADENSIS ROOT 6 [hp_X]/1 1; PULSATILLA VULGARIS 6 [hp_X]/1 1; SILICON DIOXIDE 6 [hp_X]/1 1
INACTIVE INGREDIENTS: CHERRY; CITRIC ACID MONOHYDRATE; LACTOSE MONOHYDRATE; MAGNESIUM STEARATE; MALIC ACID; MALTODEXTRIN; MANNITOL; CROSCARMELLOSE SODIUM; SORBITOL; STEARIC ACID; XYLITOL

Allergy and Sinus Relief

Active Ingredient

Pelargonium sidoides 1X

Hydrastis canadensis 6X

Kali muriaticum 3X

Sanguinaria canadensis 6X

Pulsatilla 6X

Silicea 6X

Inactive Ingredient

Citric Acid

Lactose Monohydrate

Magnesium Stearate

Malic Acid

Maltodextrin

Mannitol

Natural Flavor

Sodium Croscarmellose

Sorbitol

Sour Cherry Powder

Stearic acid

Xylitol

Purpose

Temporarily relieves allergy and sinus symptoms.

Shortens duration and reduces severity of symptoms associated with the common cold and throat, nasal, bronchial irritations: cough, headache, hoarseness, sore throat, sinus pressure, chest congestion, nasal congestion, sneezing/runny nose, shrinks swollen nasal membranes, promotes sinus drainage, burning, itchy eyes, helps decongest sinus openings and passages.

Indications & Usage

Temporarily relieves allergy and sinus symptoms.

Shortens duration and reduces severity of symptoms associated with the common cold and throat, nasal, bronchial irritations: cough, headache, hoarseness, sore throat, sinus pressure, chest congestion, nasal congestion, sneezing/runny nose, shrinks swollen nasal membranes, promotes sinus drainage, burning, itchy eyes, helps decongest sinus openings and passages.

Dosage & Administration

Directions

Chew or dissolve tablets in the mouth. Do not swallow whole. For best results, use at the first sign of symptoms and continue to use for an additional 48 hours after symptoms cease.

Adults & Children 13 years of age and older: Take 1 chewable tablet three times daily.

Children 6-12 years of age: Take 1 chewable tablet two times daily.

Children under 6 years of age: Consult a doctor.

Warnings

Sore throat warning: if sore throat is severe, persists more than 2 days, is accompanied or followed by a fever, headache, rash, nausea, or vomiting, consult a doctor promptly.

Ask Doctor

Ask a doctor before use if you have a persistent or chronic cough such as occurs with smoking, asthma, chronic bronchitis, or emphysema, a cough that is accompanied by excessive phlegm (mucus), been taking any medications, an allergy to plants of the Geraniaceae family

Stop Use

Stop use and ask a doctor if new symptoms occur, symptoms get worse or last more than 7 days, fever worsens or lasts more than 3 days, cough lasts more than 7 days or occurs with rash or persistent headache.

These could be signs of a serious condition.

Pregnancy or Breast Feeding

If pregnant or breast-feeding, ask a healthcare professional before use.

Keep out of reach of children

Overdose

In case of overdose, seek medical help or contact a Poison Control center right away.